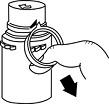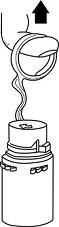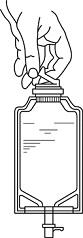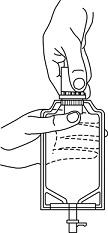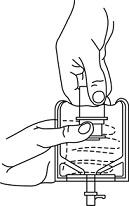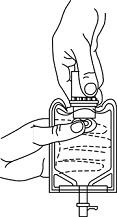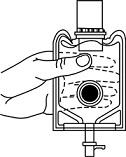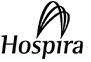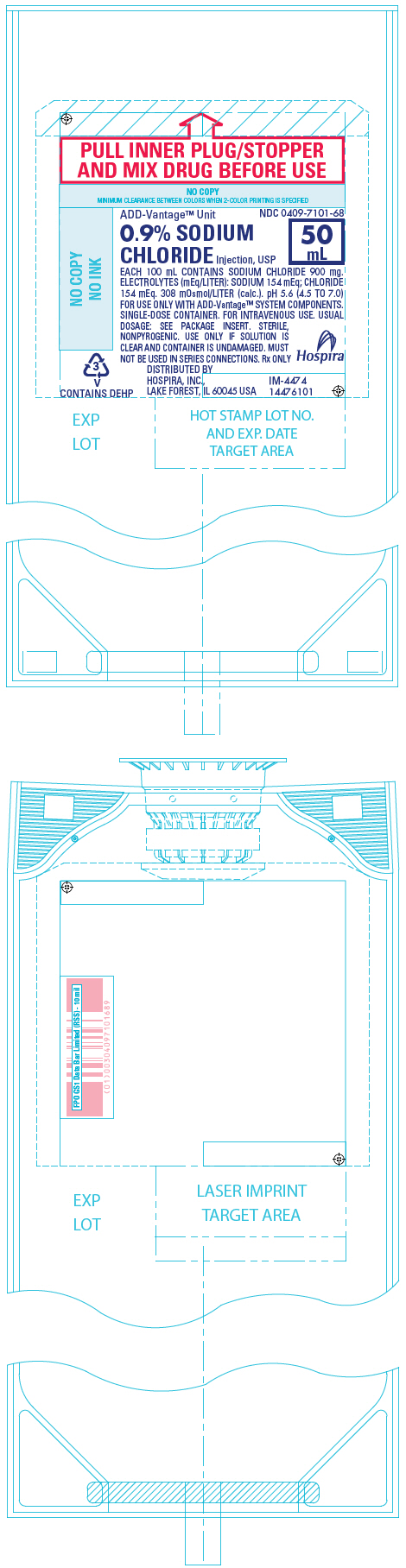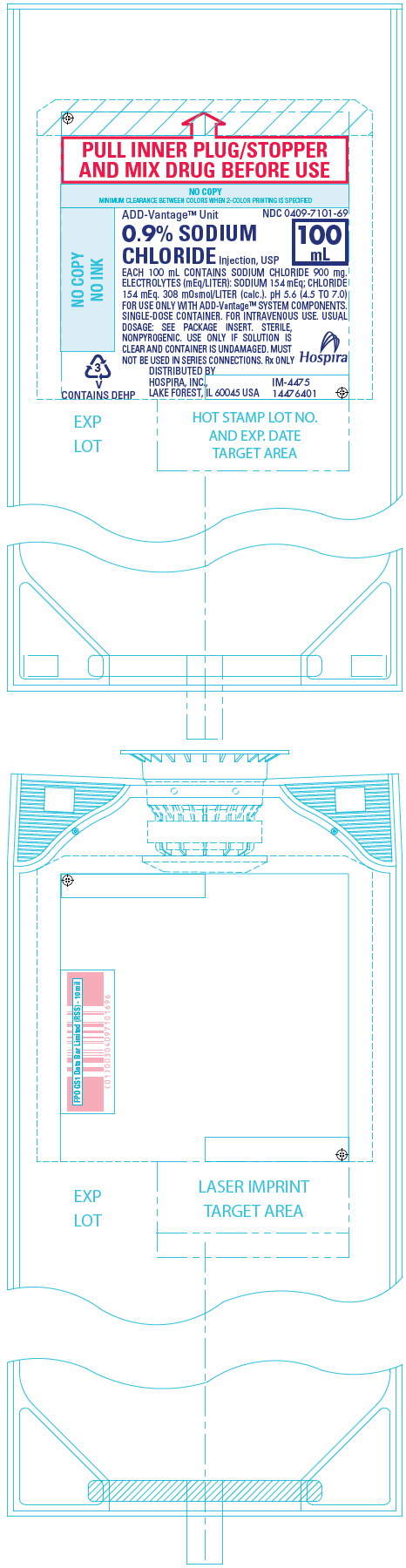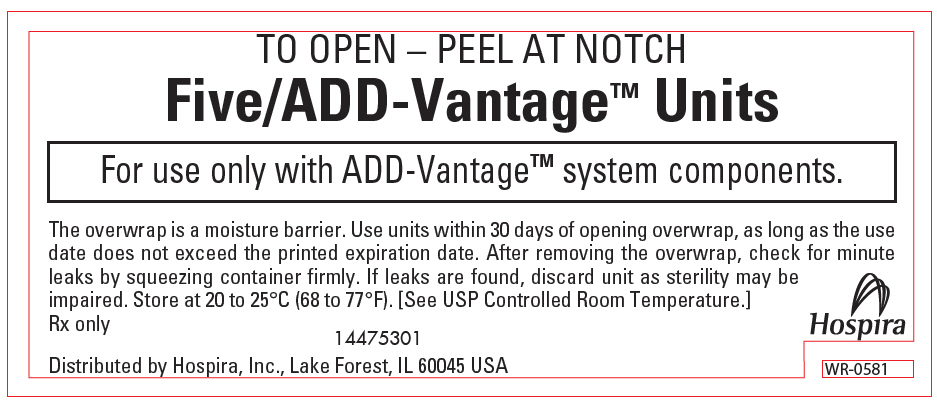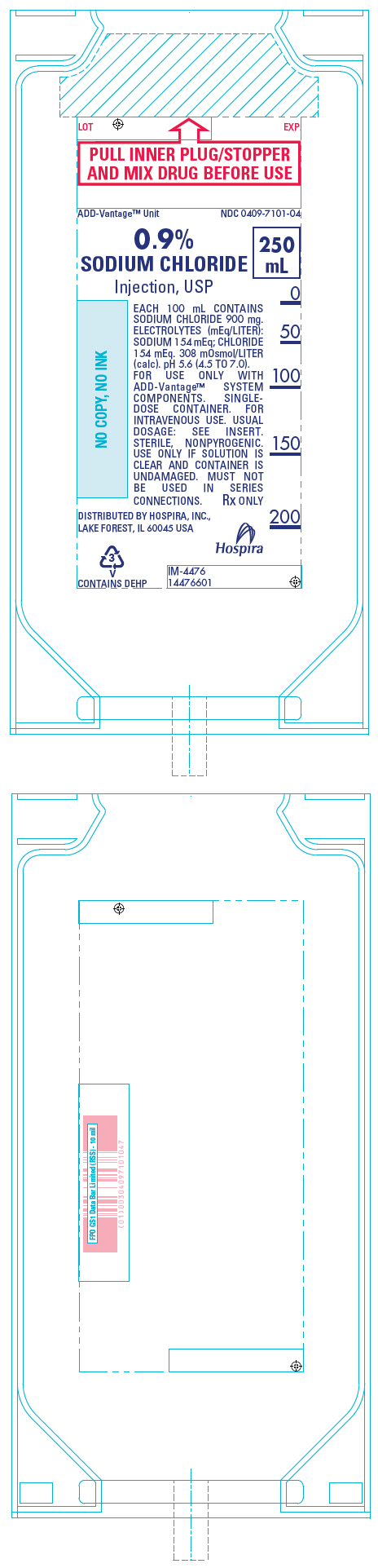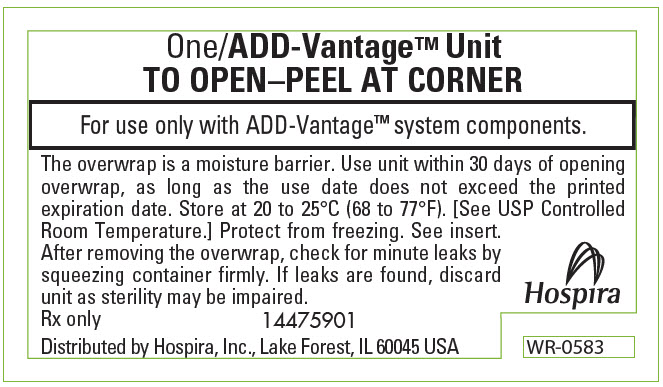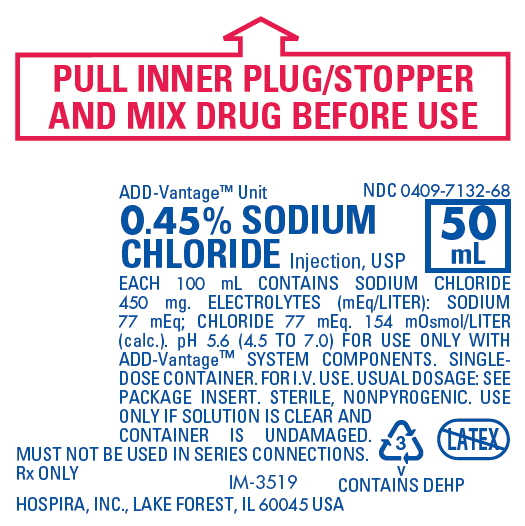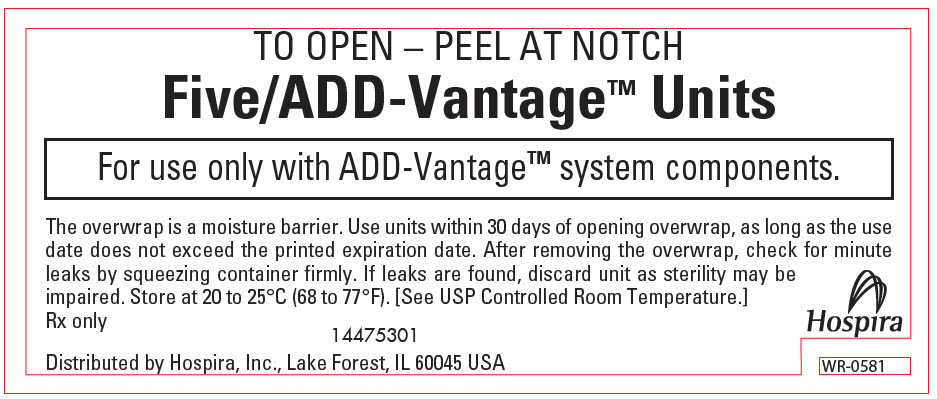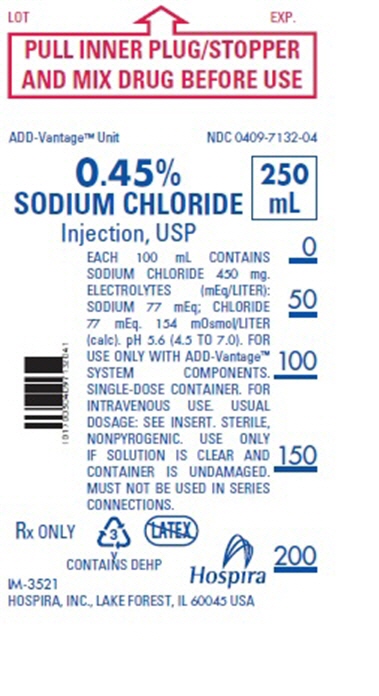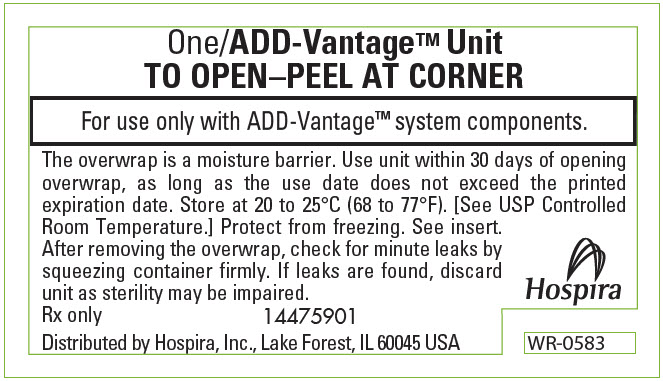 DRUG LABEL: Sodium Chloride
NDC: 0409-7101 | Form: INJECTION, SOLUTION
Manufacturer: Hospira, Inc.
Category: prescription | Type: HUMAN PRESCRIPTION DRUG LABEL
Date: 20260129

ACTIVE INGREDIENTS: SODIUM CHLORIDE 900 mg/100 mL
INACTIVE INGREDIENTS: WATER

SODIUM CHLORIDE

Injection, USP Rx only
ADD-Vantage™ Diluent
Flexible Plastic Container

DESCRIPTION

Sodium Chloride Injection, USP solutions are sterile and nonpyrogenic. They are parenteral solutions containing various concentrations of sodium chloride in water for injection intended for intravenous administration after admixing with an ADD-Vantage vial, or single-dose powdered drug vials with 20 mm closure using the ADD-Vantage ADDAPTOR™ (WARNING: DO NOT USE WITH CHEMOTHERAPY AGENTS).

Each 100 mL of 0.45% Sodium Chloride Injection, USP contains 450 mg sodium chloride in water for injection. Electrolytes per 1000 mL: sodium 77 mEq; chloride 77 mEq. The osmolarity is 154 mOsmol/L (calc.), which is hypotonic.

Each 100 mL of 0.9% Sodium Chloride Injection, USP contains 900 mg sodium chloride in water for injection. Electrolytes per 1000 mL: sodium 154 mEq; chloride 154 mEq. The osmolarity is 308 mOsmol/L (calc.), which is isotonic.

The pH for both concentrations is 5.6 (4.5 to 7.0).

The solutions contain no bacteriostat, antimicrobial agent or added buffer and each is intended only as a single-dose injection. When smaller doses are required the unused portion should be discarded.

The solutions are parenteral fluid and electrolyte replenishers.

Sodium Chloride, USP is chemically designated NaCl, a white crystalline powder freely soluble in water.

Water for Injection, USP is chemically designated H2O.

The flexible plastic container is fabricated from a specially formulated polyvinylchloride. Water can permeate from inside the container into the overwrap but not in amounts sufficient to affect the solution significantly. Solutions in contact with the plastic container may leach out certain chemical components from the plastic in very small amounts; however, biological testing was supportive of the safety of the plastic container materials. Exposure to temperatures above 25°C/77°F during transport and storage will lead to minor losses in moisture content. Higher temperatures lead to greater losses. It is unlikely that these minor losses will lead to clinically significant changes within the expiration period.

CLINICAL PHARMACOLOGY

When administered intravenously, these solutions provide a source of water and electrolytes.

Solutions which provide an isotonic concentration of sodium chloride are suitable for parenteral maintenance or replacement of water and electrolyte requirements.

Isotonic concentrations of sodium chloride are suitable for parenteral replacement of chloride losses that exceed or equal the sodium loss. Sodium chloride in water dissociates to provide sodium (Na^+) and chloride (Cl‾) ions. Sodium (Na^+) is the principal cation of the extracellular fluid and plays a large part in the therapy of fluid and electrolyte disturbances. Chloride (Cl‾) has an integral role in buffering action when oxygen and carbon dioxide exchange occurs in the red blood cells. The distribution and excretion of sodium (Na^+) and chloride (Cl‾) are largely under the control of the kidney which maintains a balance between intake and output.

Water is an essential constituent of all body tissues and accounts for approximately 70% of total body weight. Average normal adult daily requirements range from two to three liters (1.0 to 1.5 liters each for insensible water loss by perspiration and urine production).

Water balance is maintained by various regulatory mechanisms. Water distribution depends primarily on the concentration of electrolytes in the body compartments and sodium (Na^+) plays a major role in maintaining physiologic equilibrium.

INDICATIONS AND USAGE

Intravenous solutions containing sodium chloride are indicated for parenteral replenishment of fluid and sodium chloride as required by the clinical condition of the patient.

In this dosage form, Sodium Chloride Injection, USP is intended to be used as a diluent for the contents of an ADD-Vantage vial, or single-dose vials with 20 mm closure using the ADD-Vantage ADDAPTOR™.

CONTRAINDICATIONS

None known.

WARNINGS

Solutions containing sodium ions should be used with great care, if at all, in patients with congestive heart failure, severe renal insufficiency and in clinical states in which there exists edema with sodium retention.

Excessive administration of potassium-free solutions may result in significant hypokalemia.

In patients with diminished renal function, administration of solutions containing sodium ions may result in sodium retention.

The intravenous administration of these solutions can cause fluid and/or solute overloading resulting in dilution of serum electrolyte concentrations, overhydration, congested states or pulmonary edema.

The risk of dilutional states is inversely proportional to the electrolyte concentrations of administered parenteral solutions. The risk of solute overload causing congested states with peripheral and pulmonary edema is directly proportional to the electrolyte concentrations of such solutions.

PRECAUTIONS

General

Do not use plastic containers in series connections. Such use could result in air embolism due to residual air being drawn from the primary container before administration of the fluid from the secondary container is completed.

Use of a vented intravenous administration set with the vent in the open position could result in air embolism. Vented intravenous administration sets with the vent in the open position should not be used with flexible plastic containers.

Laboratory Tests

Clinical evaluation and periodic laboratory determinations are necessary to monitor changes in fluid balance, electrolyte concentrations and acid-base balance during prolonged parenteral therapy or whenever the condition of the patient warrants such evaluation.

DRUG INTERACTIONS

Caution must be exercised in the administration of parenteral fluids, especially those containing sodium ions to patients receiving corticosteroids or corticotropin.

Carcinogenesis, Mutagenesis, Impairment of Fertility: Studies with Sodium Chloride Injection, USP have not been performed to evaluate carcinogenic potential, mutagenic potential or effects on fertility.

Pregnancy: Teratogenic effects

Animal reproduction studies have not been conducted with Sodium Chloride Injection, USP. It is not known whether sodium chloride injection can cause fetal harm when administered to a pregnant woman or can affect reproduction capacity. Sodium Chloride Injection, USP should be given to a pregnant woman only if clearly needed.

Labor and Delivery: Studies have not been conducted to evaluate the effects of Sodium Chloride Injection, USP on labor and delivery. Caution should be exercised when administering this drug during labor and delivery.

Nursing Mothers: It is not known whether this drug is excreted in human milk. Because many drugs are excreted in human milk, caution should be exercised when Sodium Chloride Injection, USP is administered to a nursing mother.

Pediatric Use: Safety and effectiveness in children have not been established.

Geriatric Use: Clinical studies of Sodium Chloride Injection, USP did not include sufficient numbers of subjects aged 65 and over to determine whether they respond differently from younger subjects. Other reported clinical experience has not identified differences in responses between elderly and younger patients. In general, dose selection for an elderly patient should be cautious, usually starting at the low end of the dosing range, reflecting the greater frequency of decreased hepatic, renal, or cardiac function, and of concomitant disease or drug therapy.

This drug is known to be substantially excreted by the kidney, and the risk of toxic reactions to this drug may be greater in patients with impaired renal function. Because elderly patients are more likely to have decreased renal function, care should be taken in dose selection, and it may be useful to monitor renal function.

Do not administer unless solution is clear and container is undamaged. Discard unused portion.

ADVERSE REACTIONS

Reactions which may occur because of the solution or the technique of administration include febrile response, infection at the site of injection, venous thrombosis or phlebitis extending from the site of injection, extravasation and hypervolemia.

If an adverse reaction does occur, discontinue the infusion, evaluate the patient, institute appropriate therapeutic countermeasures and save the remainder of the fluid for examination if deemed necessary.

OVERDOSAGE

In the event of overhydration or solute overload, re-evaluate the patient and institute appropriate corrective measures. See WARNINGS, PRECAUTIONS, and ADVERSE REACTIONS.

DOSAGE AND ADMINISTRATION

The dose is dependent upon the age, weight and clinical condition of the patient.

Parenteral drug products should be inspected visually for particulate matter and discoloration prior to administration, whenever solution and container permit. See PRECAUTIONS.

HOW SUPPLIED

Unit of Sale | Concentration | Each
NDC 0409-7132-66; Case of 50 | 0.45% | NDC 0409-7132-68; 50 mL bags
NDC 0409-7132-67; Case of 50 | 0.45% | NDC 0409-7132-69; 100 mL bags
NDC 0409-7132-02; Case of 24 | 0.45% | NDC 0409-7132-04; 250 mL bags
NDC 0409-7101-66; Case of 50 | 0.9% | NDC 0409-7101-68; 50 mL bags
NDC 0409-7101-67; Case of 50 | 0.9% | NDC 0409-7101-69; 100 mL bags
NDC 0409-7101-02; Case of 24 | 0.9% | NDC 0409-7101-04; 250 mL bags

Store at 20 to 25°C (68 to 77°F). [See USP Controlled Room Temperature.] Protect from freezing.

INSTRUCTIONS FOR USE WITH ADD-VANTAGE VIAL

These instructions for use should be made available to the individuals who perform the reconstitution steps.

To Open:

Peel overwrap at corner and remove solution container. Use unit within 30 days of opening overwrap, as long as the use date does not exceed the printed expiration date. Some opacity of the plastic due to moisture absorption during the sterilization process may be observed. This is normal and does not affect the solution quality or safety. The opacity will diminish gradually.

To Assemble Vial and Flexible Diluent Container:

(Use Aseptic Technique)

1. Remove the protective covers from the top of the vial and the vial port on the diluent container as follows:
  a. To remove the breakaway vial cap, swing the pull ring over the top of the vial and pull down far enough to start the opening (SEE FIGURE 1), then pull straight up to remove the cap. (SEE FIGURE 2.)
    NOTE: Once the breakaway cap has been removed, do not access vial with syringe.

Fig. 1 Fig. 2

  b. To remove the vial port cover, grasp the tab on the pull ring, pull up to break the three tie strings, then pull back to remove the cover. (SEE FIGURE 3.)
2. Screw the vial into the vial port until it will go no further. THE VIAL MUST BE SCREWED IN TIGHTLY TO ASSURE A SEAL. This occurs approximately 1/2 turn (180°) after the first audible click. (SEE FIGURE 4.) The clicking sound does not assure a seal; the vial must be turned as far as it will go.
  NOTE: Once vial is seated, do not attempt to remove. (SEE FIGURE 4.)
3. Recheck the vial to assure that it is tight by trying to turn it further in the direction of assembly.
4. Label appropriately.

Fig. 3 Fig. 4

To Reconstitute the Drug:

1. Squeeze the bottom of the diluent container gently to inflate the portion of the container surrounding the end of the drug vial.
2. With the other hand, push the drug vial down into the container telescoping the walls of the container. Grasp the inner cap of the vial through the walls of the container. (SEE FIGURE 5.)
3. Pull the inner cap from the drug vial. (SEE FIGURE 6.) Verify that the rubber stopper has been pulled out, allowing the drug and diluent to mix.
4. Mix container contents thoroughly and use within the specified time.
5. Look through the bottom of the vial to verify that the stopper has been removed and complete mixing has occurred. (SEE FIGURE 7.)

If the rubber stopper is not removed from the vial and medication is not released on the first attempt, the inner cap may be manipulated back into the rubber stopper without removing the drug vial from the diluent container. Repeat steps 3 through 5.

Fig. 5 Fig. 6 Fig. 7

Preparation for Administration:

(Use Aseptic Technique)

1. Confirm the activation and admixture of vial contents.
2. Check for leaks by squeezing container firmly. If leaks are found, discard unit as sterility may be impaired.
3. Close flow control clamp of administration set.
4. Remove cover from outlet port at bottom of container.
5. Insert piercing pin of administration set into port with a twisting motion until the pin is firmly seated. NOTE: See full directions on administration set carton.
6. Lift the free end of the hanger loop on the bottom of the vial, breaking the two tie strings. Bend the loop outward to lock it in the upright position, then suspend container from hanger.
7. Squeeze and release drip chamber to establish proper fluid level in chamber.
8. Open flow control clamp and clear air from set. Close clamp.
9. Attach set to venipuncture device. If device is not indwelling, prime and make venipuncture.
10. Regulate rate of administration with flow control clamp.

WARNING: Do not use flexible container in series connections.

INSTRUCTIONS FOR USE WITH ADD-VANTAGE ADDAPTOR™

The instructions for use provided with the ADD-Vantage ADDAPTOR™ should be made available to the individuals who perform the reconstitution steps.

Distributed by Hospira, Inc., Lake Forest, IL 60045 USA

LAB-1103-2.0

Revised: 11/2018

PRINCIPAL DISPLAY PANEL - 50 mL Bag Label - NDC 0409-7101

PULL INNER PLUG/STOPPER
AND MIX DRUG BEFORE USE

ADD-Vantage™ Unit
NDC 0409-7101-68

0.9% SODIUM
CHLORIDE
Injection, USP

50
mL

EACH 100 mL CONTAINS SODIUM CHLORIDE 900 mg.
ELECTROLYTES (mEq/LITER): SODIUM 154 mEq; CHLORIDE
154 mEq. 308 mOsmol/LITER (calc.). pH 5.6 (4.5 TO 7.0)
FOR USE ONLY WITH ADD-Vantage™ SYSTEM COMPONENTS.
SINGLE-DOSE CONTAINER. FOR INTRAVENOUS USE. USUAL
DOSAGE: SEE PACKAGE INSERT. STERILE,
NONPYROGENIC. USE ONLY IF SOLUTION IS
CLEAR AND CONTAINER IS UNDAMAGED. MUST
NOT BE USED IN SERIES CONNECTIONS. Rx ONLY

Hospira

3
v
CONTAINS DEHP

DISTRIBUTED BY
HOSPIRA, INC.,
LAKE FOREST, IL 60045 USA

IM-4474
14476101

PRINCIPAL DISPLAY PANEL - 100 mL Bag Label - NDC 0409-7101

PULL INNER PLUG/STOPPER
AND MIX DRUG BEFORE USE

ADD-Vantage™ Unit
NDC 0409-7101-69

0.9% SODIUM
CHLORIDE
Injection, USP

100
mL

EACH 100 mL CONTAINS SODIUM CHLORIDE 900 mg.
ELECTROLYTES (mEq/LITER): SODIUM 154 mEq; CHLORIDE
154 mEq. 308 mOsmol/LITER (calc.). pH 5.6 (4.5 TO 7.0)
FOR USE ONLY WITH ADD-Vantage™ SYSTEM COMPONENTS.
SINGLE-DOSE CONTAINER. FOR INTRAVENOUS USE. USUAL
DOSAGE: SEE PACKAGE INSERT. STERILE,
NONPYROGENIC. USE ONLY IF SOLUTION IS
CLEAR AND CONTAINER IS UNDAMAGED. MUST
NOT BE USED IN SERIES CONNECTIONS. Rx ONLY

Hospira

3
v
CONTAINS DEHP

DISTRIBUTED BY
HOSPIRA, INC.,
LAKE FOREST, IL 60045 USA

IM-4475
14476401

PRINCIPAL DISPLAY PANEL - 50 ML AND 100 ML BAG OVERWRAP LABEL – NDC 0409-7101

TO OPEN – PEEL AT NOTCH

Five/ADD-Vantage™ Units

For use only with ADD-Vantage™ system components.

The overwrap is a moisture barrier. Use units within 30 days of opening overwrap, as long as the use
date does not exceed the printed expiration date. After removing the overwrap, check for minute
leaks by squeezing container firmly. If leaks are found, discard unit as sterility may be
impaired. Store at 20 to 25°C (68 to 77°F). [See USP Controlled Room Temperature.]

Rx only

14475301

Distributed by Hospira, Inc., Lake Forest, IL 60045 USA

Hospira

WR-0581

PRINCIPAL DISPLAY PANEL - 250 mL Bag Label - NDC 0409-7101

LOT
EXP.

PULL INNER PLUG/STOPPER
AND MIX DRUG BEFORE USE

ADD-Vantage™ Unit
NDC 0409-7101-04

0.9%
SODIUM CHLORIDE
Injection, USP

250
mL

EACH 100 mL CONTAINS
SODIUM CHLORIDE 900 mg.
ELECTROLYTES (mEq/LITER):
SODIUM 154 mEq; CHLORIDE
154 mEq. 308 mOsmol/LITER
(calc). pH 5.6 (4.5 TO 7.0).
FOR USE ONLY WITH
ADD-Vantage™ SYSTEM
COMPONENTS. SINGLE-
DOSE CONTAINER. FOR
INTRAVENOUS USE. USUAL
DOSAGE: SEE INSERT.
STERILE, NONPYROGENIC.
USE ONLY IF SOLUTION IS
CLEAR AND CONTAINER IS
UNDAMAGED. MUST NOT
BE USED IN SERIES
CONNECTIONS.
Rx ONLY

DISTRIBUTED BY HOSPIRA, INC.,
LAKE FOREST, IL 60045 USA

Hospira

3
v
CONTAINS DEHP

IM-4476
14476601

PRINCIPAL DISPLAY PANEL - 250 mL Bag Overwrap Label - NDC 0409-7101

One/ADD-Vantage™ Unit
TO OPEN–PEEL AT CORNER

For use only with ADD-Vantage™ system components.

The overwrap is a moisture barrier. Use unit within 30 days of opening
overwrap, as long as the use date does not exceed the printed
expiration date. Store at 20 to 25°C (68 to 77°F). [See USP Controlled
Room Temperature.] Protect from freezing. See insert.
After removing the overwrap, check for minute leaks by
squeezing container firmly. If leaks are found, discard
unit as sterility may be impaired.

Rx only

14475901

Distributed by Hospira, Inc., Lake Forest, IL 60045 USA

Hospira

WR-0583

PRINCIPAL DISPLAY PANEL - 50 mL Bag Label - NDC 0409-7132

PULL INNER PLUG/STOPPER
AND MIX DRUG BEFORE USE

ADD-Vantage™ Unit
NDC 0409-7132-68

0.45% SODIUM
CHLORIDE Injection, USP

50
mL

EACH 100 mL CONTAINS SODIUM CHLORIDE
450 mg. ELECTROLYTES (mEq/LITER): SODIUM
77 mEq; CHLORIDE 77 mEq. 154 mOsmol/LITER
(calc.). pH 5.6 (4.5 TO 7.0) FOR USE ONLY WITH
ADD-Vantage™ SYSTEM COMPONENTS. SINGLE-
DOSE CONTAINER. FOR I.V. USE. USUAL DOSAGE: SEE
PACKAGE INSERT. STERILE, NONPYROGENIC. USE
ONLY IF SOLUTION IS CLEAR AND
CONTAINER IS UNDAMAGED.
MUST NOT BE USED IN SERIES CONNECTIONS.

3
v
CONTAINS DEHP

Rx ONLY

IM-3519

HOSPIRA, INC., LAKE FOREST, IL 60045 USA

PRINCIPAL DISPLAY PANEL - 50 mL Bag Overwrap Label - NDC 0409-7132

TO OPEN – PEEL AT NOTCH

Five/ADD-Vantage™ Units

For use only with ADD-Vantage™ system components.

The overwrap is a moisture barrier. Use units within 30 days of opening overwrap, as long as the use
date does not exceed the printed expiration date. After removing the overwrap, check for minute
leaks by squeezing container firmly. If leaks are found, discard unit as sterility may be
impaired. Store at 20 to 25°C (68 to 77°F). [See USP Controlled Room Temperature.]

Rx only

14475301

Distributed by Hospira, Inc., Lake Forest, IL 60045 USA

Hospira

WR-0581

PRINCIPAL DISPLAY PANEL - 250 mL Bag Label - NDC 0409-7132

LOT
EXP.

PULL INNER PLUG/STOPPER
AND MIX DRUG BEFORE USE

ADD-Vantage™ Unit
NDC 0409-7132-04

0.45%
SODIUM CHLORIDE
Injection, USP

250
mL

EACH 100 mL CONTAINS
SODIUM CHLORIDE 450 mg.
ELECTROLYTES (mEq/LITER):
SODIUM 77 mEq; CHLORIDE
77 mEq. 154 mOsmol/LITER
(calc). pH 5.6 (4.5 TO 7.0). FOR
USE ONLY WITH ADD-Vantage™
SYSTEM COMPONENTS.
SINGLE-DOSE CONTAINER. FOR
INTRAVENOUS USE. USUAL
DOSAGE: SEE INSERT. STERILE,
NONPYROGENIC. USE ONLY
IF SOLUTION IS CLEAR AND
CONTAINER IS UNDAMAGED.
MUST NOT BE USED IN SERIES
CONNECTIONS.

Rx ONLY

3
v
CONTAINS DEHP

IM-3521
HOSPIRA, INC., LAKE FOREST, IL 60045 USA
Hospira

PRINCIPAL DISPLAY PANEL - 250 mL Bag Overwrap Label - NDC 0409-7132

One/ADD-Vantage™ Unit
TO OPEN–PEEL AT CORNER

For use only with ADD-Vantage™ system components.

The overwrap is a moisture barrier. Use unit within 30 days of opening
overwrap, as long as the use date does not exceed the printed
expiration date. Store at 20 to 25°C (68 to 77°F). [See USP Controlled
Room Temperature.] Protect from freezing. See insert.
After removing the overwrap, check for minute leaks by
squeezing container firmly. If leaks are found, discard
unit as sterility may be impaired.

Rx only

14475901

Distributed by Hospira, Inc., Lake Forest, IL 60045 USA

Hospira

WR-0583